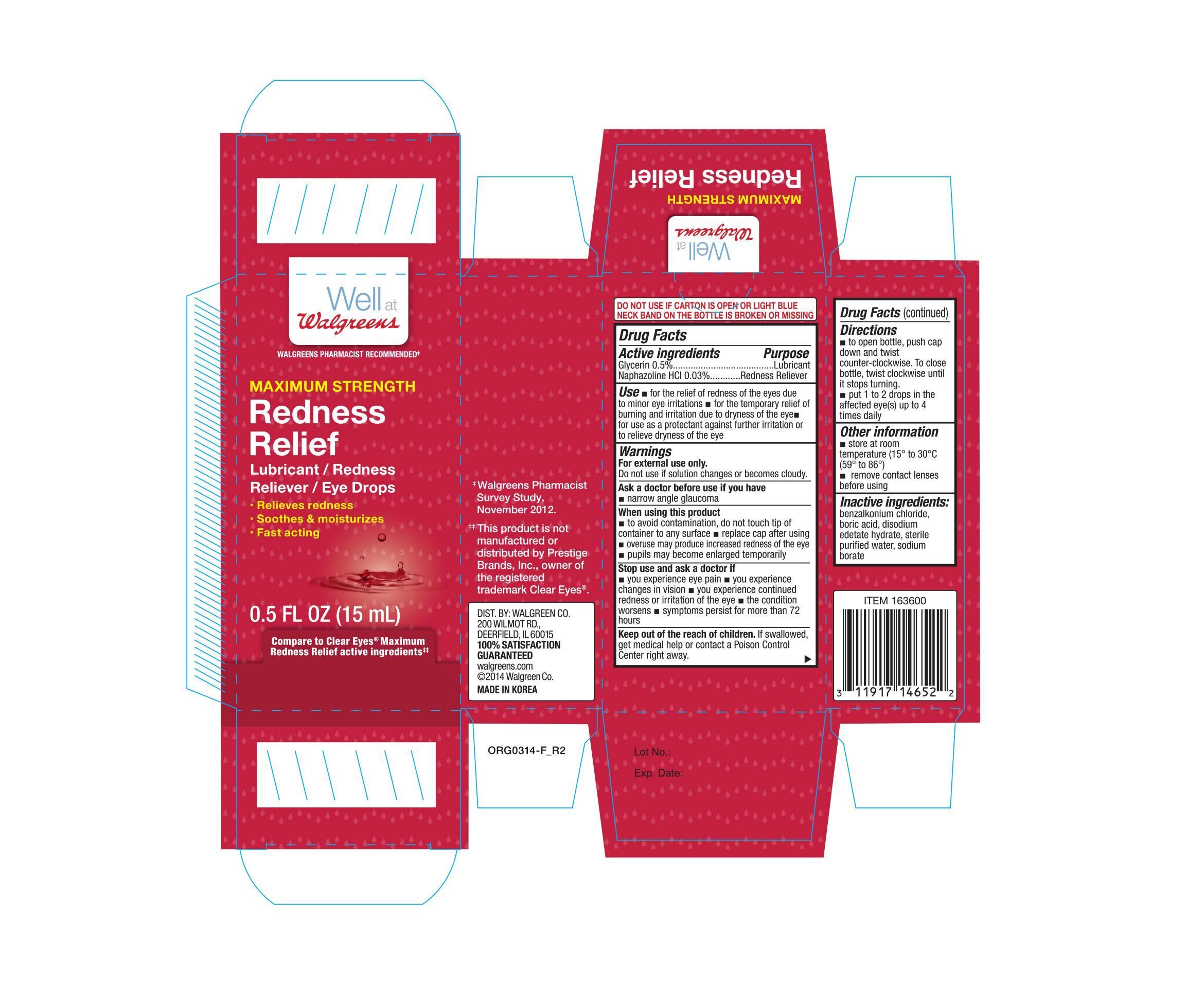 DRUG LABEL: WALGREENS MAXIMUM REDNESS RELIEF
NDC: 0363-1465 | Form: SOLUTION
Manufacturer: WALGREEN COMPANY
Category: otc | Type: HUMAN OTC DRUG LABEL
Date: 20141125

ACTIVE INGREDIENTS: GLYCERIN 0.0025 mg/1 mL; NAPHAZOLINE HYDROCHLORIDE 0.00012 mg/1 mL
INACTIVE INGREDIENTS: BENZALKONIUM CHLORIDE; EDETATE DISODIUM; BORIC ACID; SODIUM BORATE; WATER

Active ingredients Purpose

Glycerin 0.5% ................................................................. Lubricant

Naphazoline HCL 0.03% ................................................... Redness reliever

Uses

- for the relief of redness of the eye due to minor eye irritations.
- for the temporary relief of burning and irritation due to the dryness of the eye.
- for the use as a protectant against further irritation or dryness of the eye.

Warnings

For external use only.

Do not use if solution changes or becomes cloudy.

Ask a doctor before use if you have

- narrow angle glaucoma

When using this product:

- to avoid contamination, do not touch tip of container to any surface
- replace cap after using
- overuse may produce increased redness of the eye
- pupils may become enlarged temporarily

Stop use and ask a doctor if:

- you experience eye pain
- you experience changes in vision
- you experience continued redness or irritation of the eye
- the condition worsens or persists for more than 72 hours

Keep out of reach of children

If swallowed, get medical help or contact a Poison Control Center right away

Directions

- to open bottle, push cap down and twist counter-clockwise. To close bottle, twist clockwise until it stops turning.
- put 1 to 2 drops in the affected eye(s) up to 4 times daily

Other information

- store at room temperature (15° to 30°C 59° to 86°F)
- remove contact lenses before using

Inactive ingredients

benzalkonium chloride, boric acid, edetate disodium, purified water, sodium borate

DOSAGE AND ADMINISTRATION

DISTRIBUTED BY:

WALGREEN CO.

200 WILMOT RD.

DEERFIELD, IL 60015

walgreens.com

Made in Korea